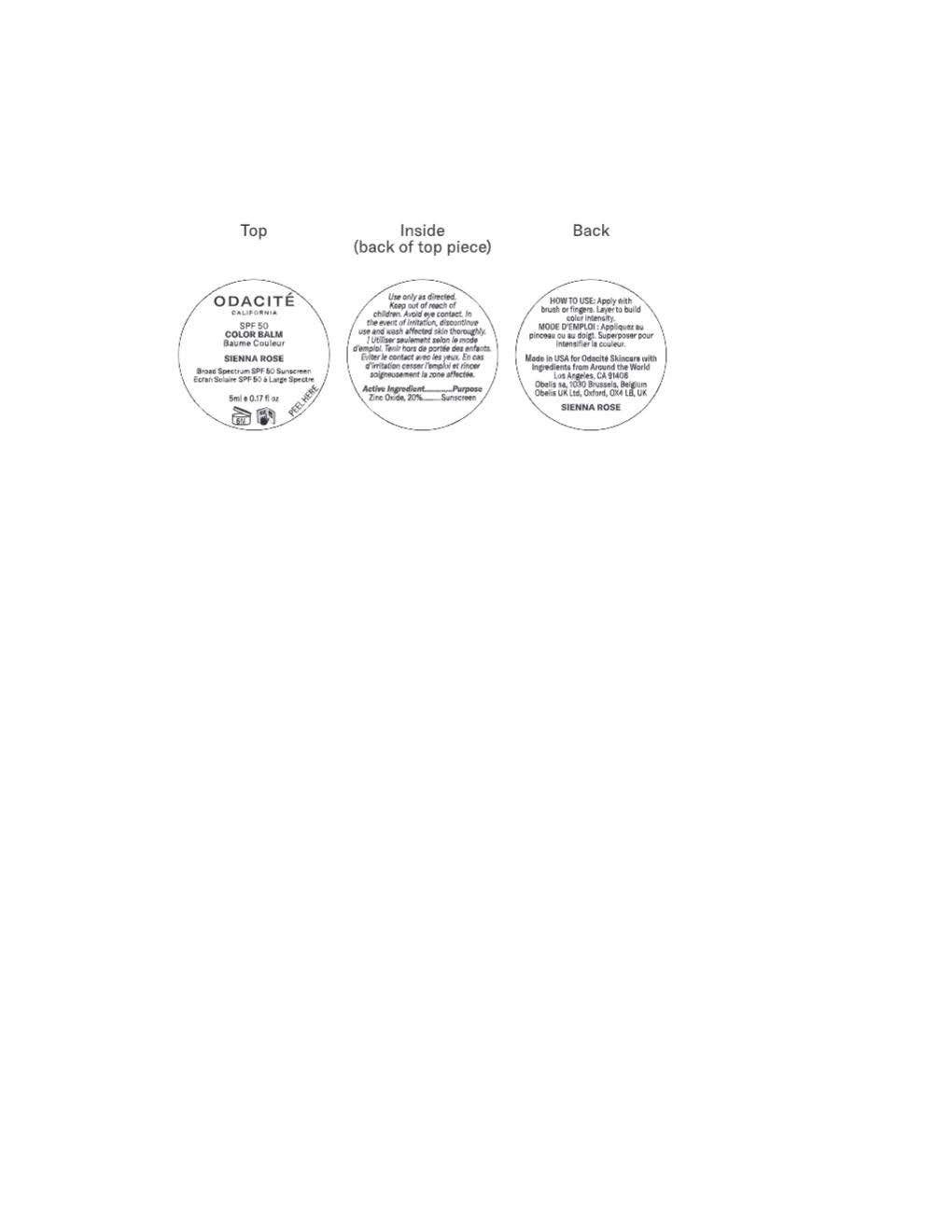 DRUG LABEL: Odacite Color Balm
NDC: 82088-250 | Form: LOTION
Manufacturer: Odacite
Category: otc | Type: HUMAN OTC DRUG LABEL
Date: 20251104

ACTIVE INGREDIENTS: ZINC OXIDE 220 mg/1 mL
INACTIVE INGREDIENTS: POLYGLYCERYL-2 DIPOLYHYDROXYSTEARATE; LECITHIN, SOYBEAN; CAPRYLYL METHICONE; POLYGLYCERYL-3 RICINOLEATE; CAPRYLIC/CAPRIC TRIGLYCERIDE; POLYGLYCERYL-3 DIISOSTEARATE; SILICON DIOXIDE; TOCOPHEROL; ISOHEXADECANE; TIN OXIDE; FERROSOFERRIC OXIDE; BUTYLOCTYL SALICYLATE; MICA; ISODODECANE; FERRIC OXIDE YELLOW; TITANIUM DIOXIDE; POLYMETHYLSILSESQUIOXANE (4.5 MICRONS); C13-15 ALKANE; TRIETHOXYCAPRYLYLSILANE; FERRIC OXIDE RED; CALCIUM SODIUM BOROSILICATE

Odacite Color Balm